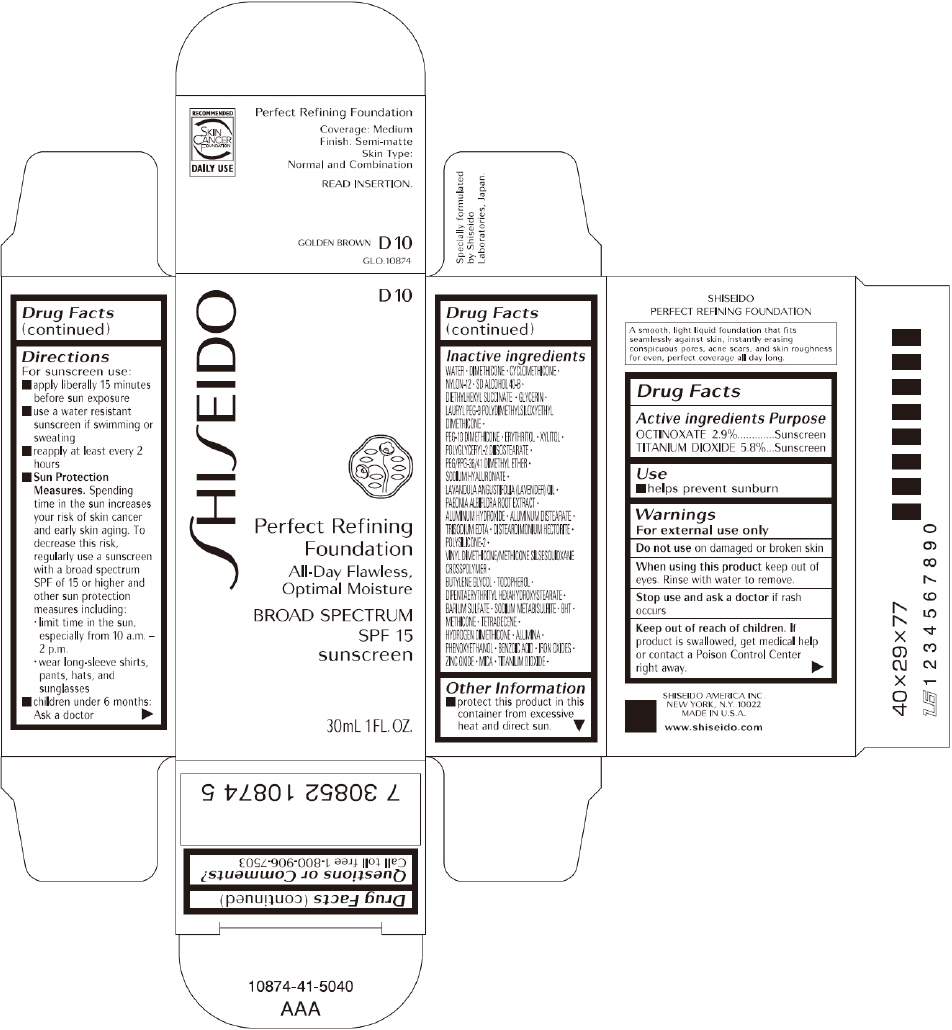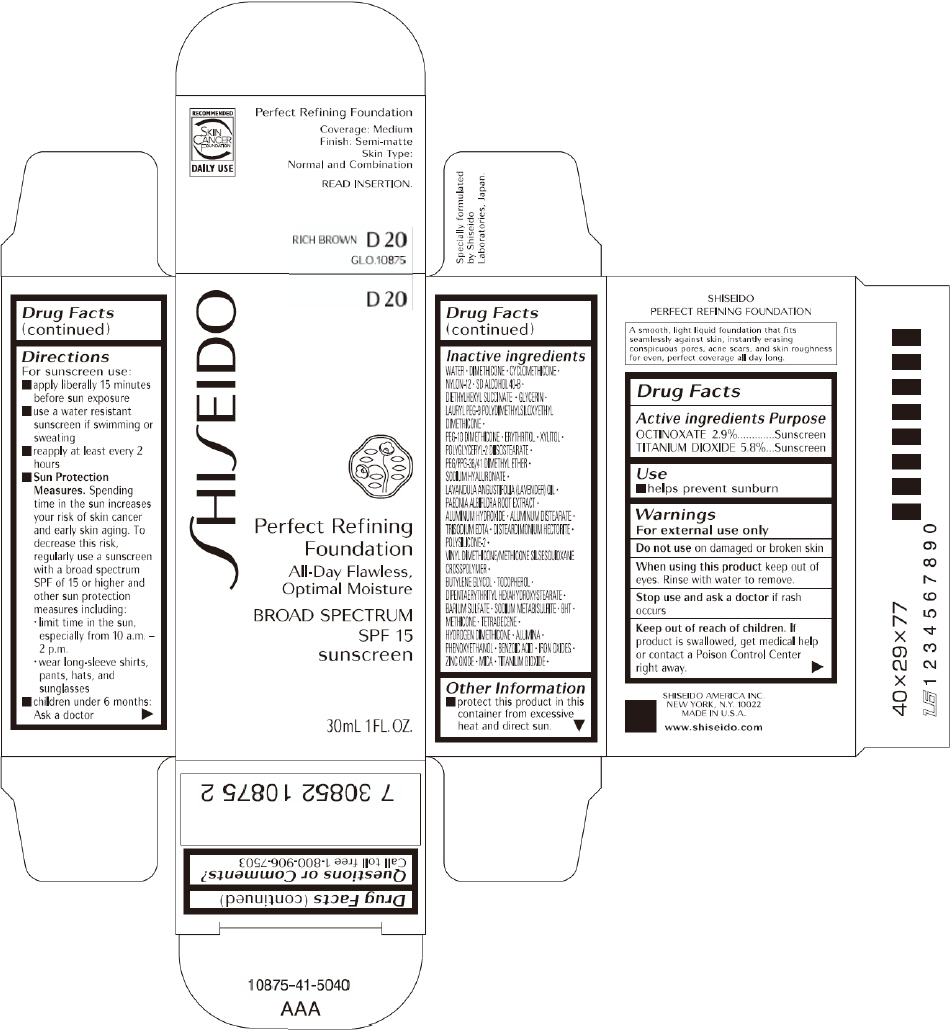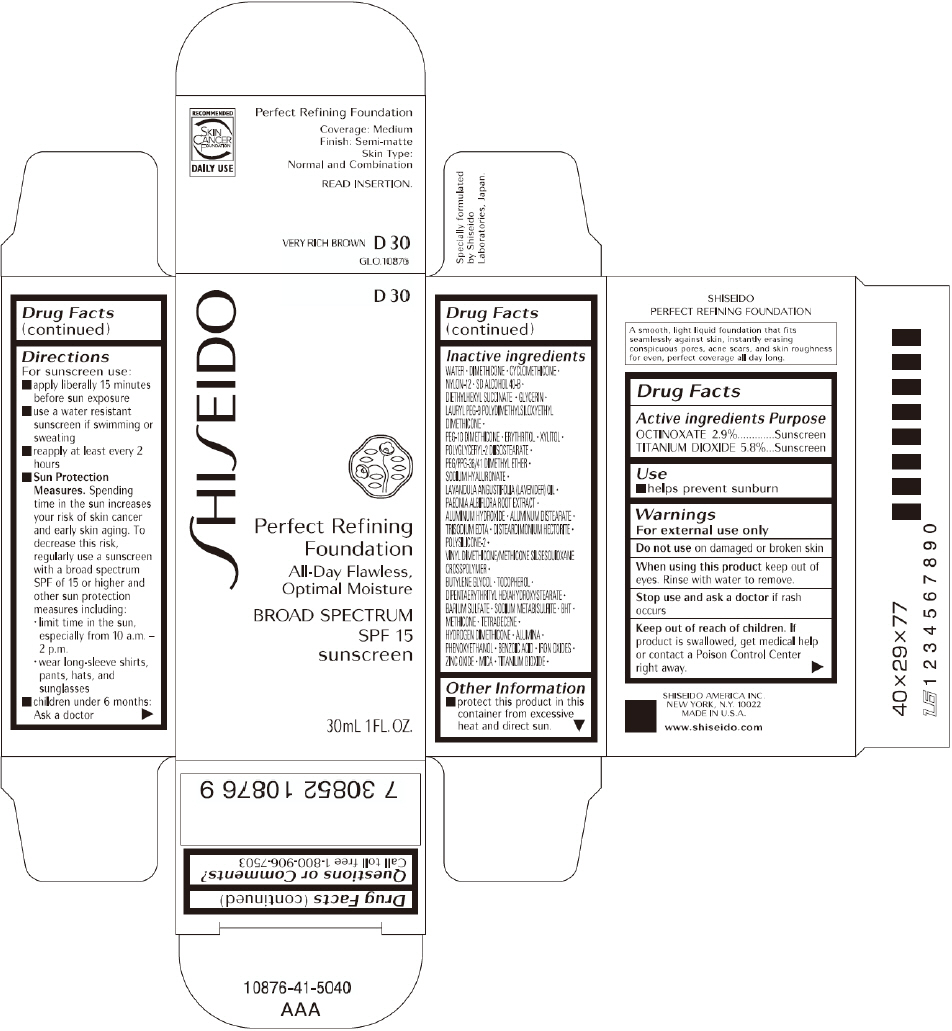 DRUG LABEL: SHISEIDO PERFECT REFINING FOUNDATION
NDC: 52686-277 | Form: CREAM
Manufacturer: SHISEIDO AMERICA INC.
Category: otc | Type: HUMAN OTC DRUG LABEL
Date: 20181219

ACTIVE INGREDIENTS: OCTINOXATE 983 mg/33.9 g; TITANIUM DIOXIDE 1966 mg/33.9 g
INACTIVE INGREDIENTS: WATER; DIMETHICONE; CYCLOMETHICONE; NYLON-12; FERRIC OXIDE RED; FERRIC OXIDE YELLOW; FERROSOFERRIC OXIDE; DIETHYLHEXYL SUCCINATE; GLYCERIN; PEG-10 DIMETHICONE (600 CST); ERYTHRITOL; XYLITOL; ALUMINUM HYDROXIDE; ALUMINUM DISTEARATE; PHENOXYETHANOL; EDETATE TRISODIUM; PEG/PPG-36/41 DIMETHYL ETHER; HYALURONATE SODIUM; BUTYLENE GLYCOL; .ALPHA.-TOCOPHEROL; ZINC OXIDE; MICA; DIPENTAERYTHRITYL HEXAHYDROXYSTEARATE; BARIUM SULFATE; SODIUM METABISULFITE; LAVENDER OIL; PAEONIA LACTIFLORA ROOT; BUTYLATED HYDROXYTOLUENE; METHICONE (20 CST); TETRADECENE; ALUMINUM OXIDE; BENZOIC ACID

SHISEIDO PERFECT REFINING FOUNDATION (D10, D20, D30)

Drug Facts

ACTIVE INGREDIENT

ACTIVE INGREDIENTS: | Purpose
OCTINOXATE 2.9% | Sunscreen
TITANIUM DIOXIDE 5.8% | Sunscreen

Use

- helps prevent sunburn

Warnings

For external use only

Do not use on damaged or broken skin

When using this product keep out of eyes. Rinse with water to remove.

Stop use and ask a doctor if rash occurs

Keep out of reach of children. If product is swallowed, get medical help or contact a Poison Control Center right away.

Directions

For sunscreen use:

- apply liberally 15 minutes before sun exposure
- use a water resistant sunscreen if swimming or sweating
- reapply at least every 2 hours
- Sun Protection Measures. Spending time in the sun increases your risk of skin cancer and early skin aging. To decrease this risk, regularly use a sunscreen with a broad spectrum SPF of 15 or higher and other sun protection measures including:
  - limit time in the sun, especially from 10 a.m. – 2 p.m.
  - wear long-sleeve shirts, pants, hats, and sunglasses
- children under 6 months: Ask a doctor

Inactive Ingredients

WATER, DIMETHICONE, CYCLOMETHICONE, NYLON-12, SD ALCOHOL 40-B, DIETHYLHEXYL SUCCINATE, GLYCERIN, LAURYL PEG-9 POLYDIMETHYLSILOXYETHYL DIMETHICONE, PEG-10 DIMETHICONE, ERYTHRITOL, XYLITOL, POLYGLYCERYL-2 DIISOSTEARATE, PEG/PPG-36/41 DIMETHYL ETHER, SODIUM HYALURONATE, LAVANDULA ANGUSTIFOLIA (LAVENDER) OIL, PAEONIA ALBIFLORA ROOT EXTRACT, ALUMINUM HYDROXIDE, ALUMINUM DISTEARATE, TRISODIUM EDTA, DISTEARDIMONIUM HECTORITE, POLYSILICONE-2, VINYL DIMETHICONE/METHICONE SILSESQUIOXANE CROSSPOLYMER, BUTYLENE GLYCOL, TOCOPHEROL, DIPENTAERYTHRITYL HEXAHYDROXYSTEARATE, BARIUM SULFATE, SODIUM METABISULFITE, BHT, METHICONE, TETRADECENE, HYDROGEN DIMETHICONE, ALUMINA, PHENOXYETHANOL, BENZOIC ACID, IRON OXIDES, ZINC OXIDE, MICA, TITANIUM DIOXIDE,

Other information

- protect this product in this container from excessive heat and direct sun.

Questions or comments?

Call toll free 1-800-906-7503

SHISEIDO AMERICA INC.
NEW YORK, N.Y. 10022

PRINCIPAL DISPLAY PANEL - 30mL D 10 Tube Carton

SHISEIDO

D 10

Perfect Refining
Foundation

All-Day Flawless,
Optimal Moisture

BROAD SPECTRUM
SPF 15
sunscreen

30mL 1 FL. OZ.

PRINCIPAL DISPLAY PANEL - 30mL D 20 Tube Carton

SHISEIDO

D 20

Perfect Refining
Foundation

All-Day Flawless,
Optimal Moisture

BROAD SPECTRUM
SPF 15
sunscreen

30mL 1 FL. OZ.

PRINCIPAL DISPLAY PANEL - 30mL D 30 Tube Carton

SHISEIDO

D 30

Perfect Refining
Foundation

All-Day Flawless,
Optimal Moisture

BROAD SPECTRUM
SPF 15
sunscreen

30mL 1 FL. OZ.